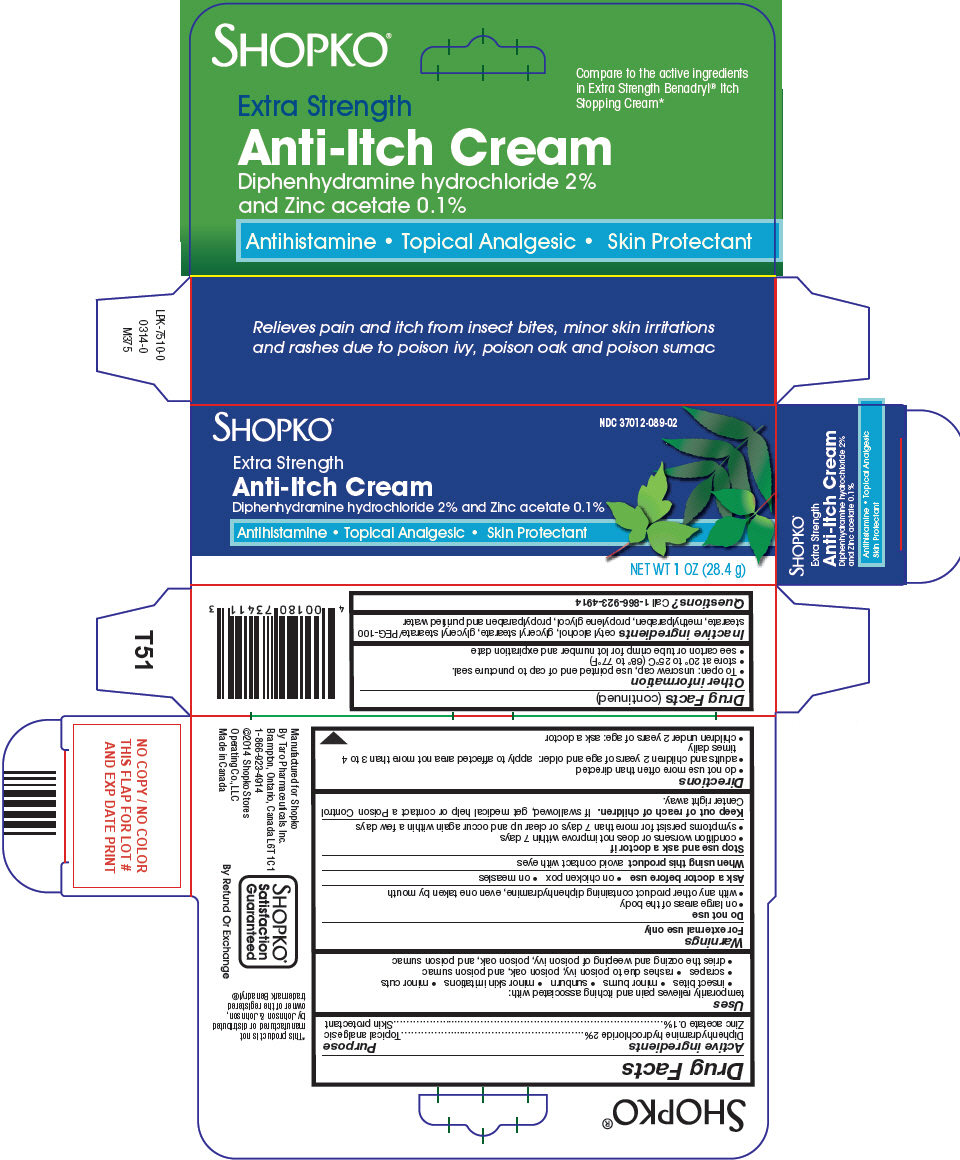 DRUG LABEL: Shopko Anti-Itch
NDC: 37012-089 | Form: CREAM
Manufacturer: Shopko Stores Operating Co., LLC
Category: otc | Type: HUMAN OTC DRUG LABEL
Date: 20250714

ACTIVE INGREDIENTS: DIPHENHYDRAMINE HYDROCHLORIDE 20 mg/1 g; ZINC ACETATE 1 mg/1 g
INACTIVE INGREDIENTS: CETYL ALCOHOL; GLYCERYL MONOSTEARATE; PEG-100 STEARATE; METHYLPARABEN; PROPYLENE GLYCOL; PROPYLPARABEN; WATER

Shopko®Anti-Itch Cream

Drug Facts

ACTIVE INGREDIENT

Active ingredients | Purpose
Diphenhydramine hydrochloride 2% | Topical analgesic
Zinc acetate 0.1% | Skin protectant

Uses

temporarily relieves pain and itching associated with:

- insect bites
- minor burns
- sunburn
- minor skin irritations
- minor cuts
- scrapes
- rashes due to poison ivy, poison oak, and poison sumac
- dries the oozing and weeping of poison ivy, poison oak, and poison sumac

Warnings

For external use only

Do not use

- on large areas of the body
- with any other product containing diphenhydramine, even one taken by mouth

Ask a doctor before use

- on chicken pox
- on measles

When using this productavoid contact with eyes

Stop use and ask a doctor if

- condition worsens or does not improve within 7 days
- symptoms persist for more than 7 days or clear up and occur again within a few days

Keep out of reach of children.If swallowed, get medical help or contact a Poison Control Center right away.

Directions

- do not use more often than directed
- adults and children 2 years of age and older: apply to affected area not more than 3 to 4 times daily
- children under 2 years of age: ask a doctor

Other information

- To open: unscrew cap, use pointed end of cap to puncture seal.
- store at 20° to 25°C (68° to 77°F)
- see carton or tube crimp for lot number and expiration date

Inactive ingredients

cetyl alcohol, glyceryl stearate, glyceryl stearate/PEG-100 stearate, methylparaben, propylene glycol, propylparaben and purified water

Questions?

Call 1-866-923-4914

PRINCIPAL DISPLAY PANEL - 28.4 g Tube Carton

SHOPKO®

NDC 37012-089-02

Extra Strength
Anti-Itch Cream
Diphenhydramine hydrochloride 2% and Zinc acetate 0.1%

Antihistamine • Topical Analgesic • Skin Protectant

NET WT 1OZ (28.4 g)